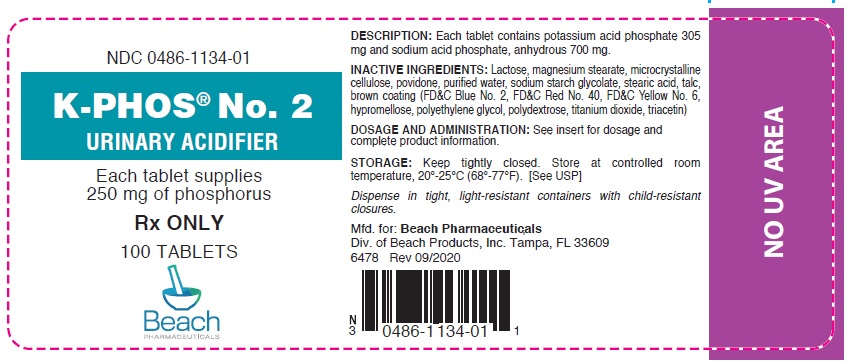 DRUG LABEL: K-Phos

NDC: 0486-1134 | Form: TABLET, COATED
Manufacturer: Beach Products, Inc.
Category: prescription | Type: HUMAN PRESCRIPTION DRUG LABEL
Date: 20230223

ACTIVE INGREDIENTS: POTASSIUM PHOSPHATE, MONOBASIC 305 mg/1 1; SODIUM PHOSPHATE, MONOBASIC, ANHYDROUS 700 mg/1 1
INACTIVE INGREDIENTS: LACTOSE; MAGNESIUM STEARATE; CELLULOSE, MICROCRYSTALLINE; WATER O-18; SODIUM STARCH GLYCOLATE TYPE A POTATO; STEARIC ACID; TALC; FD&C BLUE NO. 2; FD&C RED NO. 40; FD&C YELLOW NO. 6; HYPROMELLOSES; POLYDEXTROSE; TITANIUM DIOXIDE; TRIACETIN; POLYETHYLENE GLYCOL, UNSPECIFIED; POVIDONE K30

K-PHOS® No. 2
Urinary Acidifier

Rx ONLY

DESCRIPTION

Each tablet contains potassium acid phosphate 305 mg and sodium acid phosphate, anhydrous, 700 mg. Each tablet yields approximately 250 mg of phosphorus, 88 mg of potassium or 2.3 mEq and 134 mg of sodium or 5.8 mEq.

Inactive ingredients: Lactose, magnesium stearate, microcrystalline cellulose, povidone, purified water, sodium starch glycolate, stearic acid, talc, brown coating (FD&C Blue No. 2, FD&C Red No. 40, FD&C Yellow No. 6, hypromellose, polyethylene glycol, polydextrose, titanium dioxide, triacetin).

CLINICAL PHARMACOLOGY

Phosphorus has a number of important functions in the biochemistry of the body. The bulk of the body's phosphorus is located in the bones, where it plays a key role in osteoblastic and osteoclastic activities. Enzymatically catalyzed phosphate-transfer reactions are numerous and vital in the metabolism of carbohydrate, lipid and protein, and a proper concentration of the anion is of primary importance in assuring an orderly biochemical sequence. In addition, phosphorus plays an important role in modifying steady-state tissue concentrations of calcium. Phosphate ions are important buffers of the intracellular fluid, and also play a primary role in the renal excretion of hydrogen ion.

Oral administration of inorganic phosphates increases serum phosphate levels. Phosphates lower urinary calcium levels in idiopathic hypercalciuria.

In general, in adults, about two thirds of the ingested phosphate is absorbed from the bowel, most of which is rapidly excreted into the urine.

INDICATONS AND USAGE

K-PHOS® No. 2 is a highly effective urinary acidifier for use in patients with elevated urinary pH. This product helps keep calcium soluble and reduces odor and rash caused by ammoniacal urine. Also, by acidifying the urine, it increases the antibacterial activity of methenamine mandelate and methenamine hippurate.

CONTRAINDICATIONS

This product is contraindicated in patients with infected phosphate stones, in patients with severely impaired renal function (less than 30% of normal) and in the presence of hyperphosphatemia.

PRECAUTIONS

General

This product contains potassium and sodium and should be used with caution if regulation of these elements is desired. Occasionally, some individuals may experience a mild laxative effect during the first few days of phosphate therapy. If laxation persists to an unpleasant degree, reduce the daily dosage until this effect subsides or, if necessary, discontinue the use of this product.

Use of this medication should be carefully considered when the following medical problems exist: Cardiac disease (particularly in digitalized patients), Addison's disease, acute dehydration, extensive tissue breakdown, myotonia congenita, cardiac failure, cirrhosis of the liver or severe hepatic disease, peripheral and pulmonary edema, hypernatremia, hypertension, toxemia of pregnancy, hypoparathyroidism, and acute pancreatitis. Rickets may benefit from phosphate therapy, but caution should be observed. High serum phosphate levels increase the risk of extraskeletal calcification.

Information for Patients

Patients with kidney stones may pass old stones when phosphate therapy is started and should be warned of this possibility. Patients should be advised to avoid the use of antacids containing aluminum, magnesium, or calcium which may prevent the absorption of phosphate.

Laboratory Tests

Careful monitoring of renal function and serum calcium, phosphorus, potassium and sodium may be required at periodic intervals during phosphate therapy. Other tests may be warranted in some patients, depending on conditions.

Drug Interactions

The use of antacids containing magnesium, aluminum, or calcium in conjunction with phosphate preparations may bind the phosphate and prevent its absorption. Concurrent use of antihypertensives, especially diazoxide, guanethidine, hydralazine, methyldopa, or rauwolfia alkaloid; or corticosteroids, especially mineralocorticoids or corticotropin, with sodium phosphate may result in hypernatremia. Potassium-containing medications or potassium-sparing diuretics may cause hyperkalemia when used wi t h potassium phosphate. Patients should have serum potassium level determinations at periodic intervals. Plasma levels of salicylates may be increased since salicylate excretion is decreased in acidified urine. Administration of monobasic phosphates to patients stabilized on salicylates may lead to toxic salicylate levels.

Carcinogenesis, Mutagenesis, Impairment of Fertility

No long-term or reproduction studies in animals or humans have been performed with K-PHOS® No. 2 to evaluate its carcinogenic, mutagenic, or impairment of fertility potential.

Pregnancy

Teratogenic Effects

Pregnancy Category C

Animal reproduction studies have not been conducted with K-PHOS® No. 2. It is also not known whether this product can cause fetal harm when administered to a pregnant woman or can affect reproductive capacity. This product should be given to a pregnant woman only if clearly needed.

Nursing Mothers

It is not known whether this drug is excreted in human milk. Because many drugs are excreted in human milk, caution should be exercised when this product is administered to a nursing woman.

ADVERSE REACTIONS

Gastrointestinal upset (diarrhea, nausea, stomach pain and vomiting) may occur with phosphate therapy. Also, bone and joint pain (possible phosphate-induced osteomalacia) could occur. The following adverse effects may be observed (primarily from sodium or potassium): headaches; dizziness; mental confusion; seizures; weakness or heaviness of legs; unusual tiredness or weakness; muscle cramps; numbness, tingling, pain, or weakness of hands or feet; numbness or tingling around lips; fast or irregular heartbeat; shortness of breath or troubled breathing; swelling of feet or lower legs; unusual weight gain; low urine output; unusual thirst.

DOSAGE AND ADMINISTRATION

One tablet four times daily with a full glass of water. When the urine is difficult to acidify, administer one tablet every two hours not to exceed 8 tablets in a 24-hour period.

HOW SUPPLIED

K-PHOS® No.2 is supplied as a brown, scored, capsule-shaped tablet with the name BEACH and the number 1134 imprinted on each tablet. Bottles of 100 (NDC 0486- 1134-01).

STORAGE

Keep tightly closed. Store at controlled room temperature, 20°-25°C (68°-77°F). [See USP]

Dispense in tight, light-resistant containers with child-resistant closures.

Manufactured for: BEACH PHARMACEUTICALS, Div. of Beach Products, Inc., Tampa, FL 33609

6478 Rev 09/2020

PRINCIPAL DISPLAY PANEL - 250 mg Tablet Bottle Label

NDC 0486-1134-01

K-PHOS® No. 2
URINARY ACIDIFIER

Each tablet supplies
250 mg of phosphorus

Rx ONLY

100 TABLETS

Beach
PHARMACEUTICALS